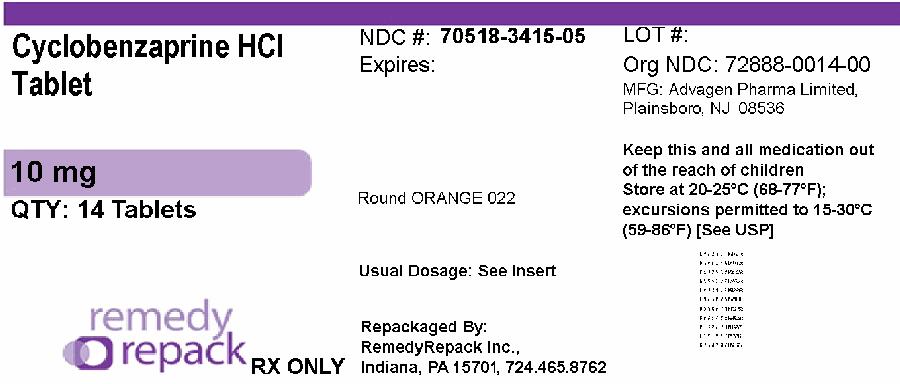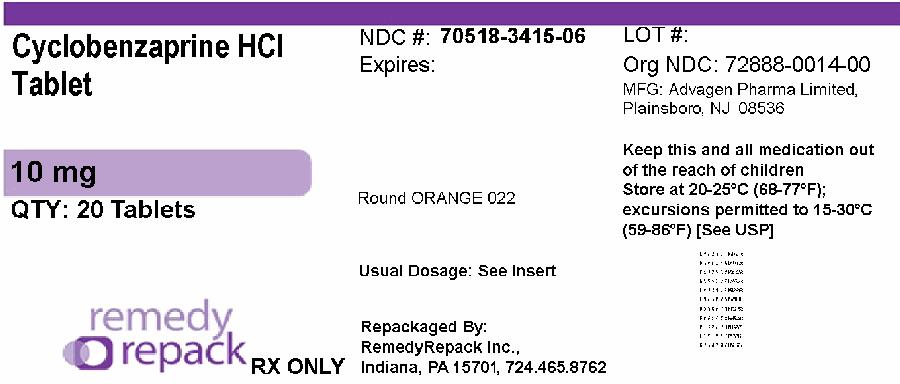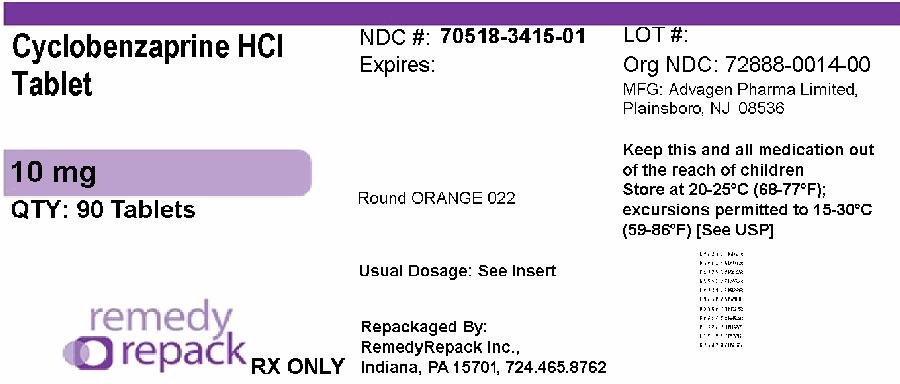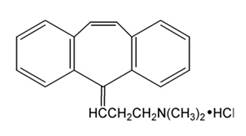 DRUG LABEL: CYCLOBENZAPRINE HYDROCHLORIDE
NDC: 70518-3415 | Form: TABLET, FILM COATED
Manufacturer: REMEDYREPACK INC.
Category: prescription | Type: HUMAN PRESCRIPTION DRUG LABEL
Date: 20260302

ACTIVE INGREDIENTS: CYCLOBENZAPRINE HYDROCHLORIDE 10 mg/1 1
INACTIVE INGREDIENTS: ANHYDROUS LACTOSE; CELLULOSE, MICROCRYSTALLINE; CROSPOVIDONE (15 MPA.S AT 5%); HYPROMELLOSE, UNSPECIFIED; MAGNESIUM STEARATE; POLYETHYLENE GLYCOL 400; POLYSORBATE 80; SILICON DIOXIDE; STARCH, CORN; TITANIUM DIOXIDE; D&C YELLOW NO. 10; FD&C YELLOW NO. 6

Cyclobenzaprine hydrochloride, USP

DESCRIPTION

Cyclobenzaprine hydrochloride, USP is a tricyclic amine salt which is white to off white, odourless, crystalline powder with the molecular formula C20H21N • HCl and a molecular weight of 311.9. It has a melting point of 217°C, and a pKa of 8.47 at 25°C. It is freely soluble in water, in alcohol and in methanol, sparingly soluble in isopropanol, slightly soluble in chloroform and in methylene chloride, insoluble in n-hexane. If aqueous solutions are made alkaline, the free base separates. Cyclobenzaprine hydrochloride is designated chemically as 3-(5H -dibenzo[a,d] cyclohepten-5-ylidene)- N,N-dimethyl-1-propanamine hydrochloride, and has the following structural formula:

Cyclobenzaprine hydrochloride tablets, USP are available as 5 mg, 7.5 mg and 10 mg tablets for oral administration. Each 5 mg, 7.5 mg and 10 mg tablet contains cyclobenzaprine hydrochloride and the following inactive ingredients: crospovidone, hypromellose, lactose anhydrous, macrogol, magnesium stearate, polysorbate 80, pregelatinized starch, silicified microcrystalline cellulose, titanium dioxide. The tablets of 5 mg and 10 mg also contain D&C Yellow #10 Aluminum Lake and FD&C Yellow #6 Sunset Yellow FCF Aluminum Lake. In addition, the 5 mg tablets contain FD&C Blue #2/INDIGO Carmine Aluminum Lake.

CLINICAL PHARMACOLOGY

Cyclobenzaprine hydrochloride relieves skeletal muscle spasm of local origin without interfering with muscle function. It is ineffective in muscle spasm due to central nervous system disease.

Cyclobenzaprine reduced or abolished skeletal muscle hyperactivity in several animal models. Animal studies indicate that cyclobenzaprine does not act at the neuromuscular junction or directly on skeletal muscle. Such studies show that cyclobenzaprine acts primarily within the central nervous system at brain stem as opposed to spinal cord levels, although its action on the latter may contribute to its overall skeletal muscle relaxant activity. Evidence suggests that the net effect of cyclobenzaprine is a reduction of tonic somatic motor activity, influencing both gamma (γ) and alpha (α) motor systems.

Pharmacological studies in animals showed a similarity between the effects of cyclobenzaprine and the structurally related tricyclic antidepressants, including reserpine antagonism, norepinephrine potentiation, potent peripheral and central anticholinergic effects, and sedation. Cyclobenzaprine caused slight to moderate increase in heart rate in animals.

Pharmacokinetics

Estimates of mean oral bioavailability of cyclobenzaprine range from 33% to 55%. Cyclobenzaprine exhibits linear pharmacokinetics over the dose range 2.5 mg to 10 mg, and is subject to enterohepatic circulation. It is highly bound to plasma proteins. Drug accumulates when dosed 3 times a day, reaching steady-state within 3 to 4 days at plasma concentrations about 4-fold higher than after a single dose. At steady-state in healthy subjects receiving 10 mg t.i.d. (n = 18), peak plasma concentration was 25.9 ng/mL (range, 12.8 to 46.1 ng/mL), and area under the concentration-time (AUC) curve over an 8-hour dosing interval was 177 ng·hr/mL (range, 80 to 319 ng·hr/mL).

Cyclobenzaprine is extensively metabolized, and is excreted primarily as glucuronides via the kidney. Cytochromes P450 3A4, 1A2, and, to a lesser extent, 2D6, mediate N-demethylation, one of the oxidative pathways for cyclobenzaprine. Cyclobenzaprine is eliminated quite slowly, with an effective half-life of 18 hours (range 8 to 37 hours; n = 18); plasma clearance is 0.7 L/min.

The plasma concentration of cyclobenzaprine is generally higher in the elderly and in patients with hepatic impairment (see PRECAUTIONS: Use in the Elderlyand PRECAUTIONS: Impaired Hepatic Function).

Elderly

In a pharmacokinetic study in elderly individuals (≥ 65 yrs old), mean (n = 10) steady-state cyclobenzaprine AUC values were approximately 1.7-fold (171 ng·hr/mL, range 96.1 to 255.3) higher than those seen in a group of 18 younger adults (101.4 ng·hr/mL, range 36.1 to 182.9) from another study. Elderly male subjects had the highest observed mean increase, approximately 2.4-fold (198.3 ng·hr/mL, range 155.6 to 255.3 vs. 83.2 ng·hr/mL, range 41.1 to 142.5 for younger males) while levels in elderly females were increased to a much lesser extent, approximately 1.2-fold (143.8 ng·hr/mL, range 96.1 to 196.3 vs. 115.9 ng·hr/mL, range 36.1 to 182.9 for younger females).

In light of these findings, therapy with cyclobenzaprine in the elderly should be initiated with a 5 mg dose and titrated slowly upward.

Hepatic Impairment

In a pharmacokinetic study of 16 subjects with hepatic impairment (15 mild, 1 moderate per Child-Pugh score), both AUC and Cmaxwere approximately double the values seen in the healthy control group. Based on the findings, cyclobenzaprine should be used with caution in subjects with mild hepatic impairment starting with the 5 mg dose and titrating slowly upward. Due to the lack of data in subjects with more severe hepatic insufficiency, the use of cyclobenzaprine in subjects with moderate to severe impairment is not recommended.

No significant effect on plasma levels or bioavailability of cyclobenzaprine or aspirin was noted when single or multiple doses of the two drugs were administered concomitantly. Concomitant administration of cyclobenzaprine and naproxen or diflunisal was well tolerated with no reported unexpected adverse effects. However combination therapy of cyclobenzaprine with naproxen was associated with more side effects than therapy with naproxen alone, primarily in the form of drowsiness. No well controlled studies have been performed to indicate that cyclobenzaprine enhances the clinical effect of aspirin or other analgesics, or whether analgesics enhance the clinical effect of cyclobenzaprine in acute musculoskeletal conditions.

Clinical Studies

Eight double-blind controlled clinical studies were performed in 642 patients comparing cyclobenzaprine hydrochloride 10 mg, diazepam, and placebo. Muscle spasm, local pain and tenderness, limitation of motion, and restriction in activities of daily living were evaluated. In three of these studies there was a significantly greater improvement with cyclobenzaprine than with diazepam, while in the other studies the improvement following both treatments was comparable.

Although the frequency and severity of adverse reactions observed in patients treated with cyclobenzaprine were comparable to those observed in patients treated with diazepam, dry mouth was observed more frequently in patients treated with cyclobenzaprine and dizziness more frequently in those treated with diazepam. The incidence of drowsiness, the most frequent adverse reaction, was similar with both drugs.

The efficacy of cyclobenzaprine hydrochloride 5 mg was demonstrated in two 7-day, double-blind, controlled clinical trials enrolling 1,405 patients. One study compared cyclobenzaprine hydrochloride 5 mg and 10 mg t.i.d. to placebo; and a second study compared cyclobenzaprine hydrochloride 5 mg and 2.5 mg t.i.d. to placebo. Primary endpoints for both trials were determined by patient-generated data and included global impression of change, medication helpfulness, and relief from starting backache. Each endpoint consisted of a score on a 5-point rating scale (from 0 or worst outcome to 4 or best outcome). Secondary endpoints included a physician's evaluation of the presence and extent of palpable muscle spasm.

Comparisons of cyclobenzaprine hydrochloride 5 mg and placebo groups in both trials established the statistically significant superiority of the 5 mg dose for all three primary endpoints at day 8 and, in the study comparing 5 mg and 10 mg, at day 3 or 4 as well. A similar effect was observed with cyclobenzaprine hydrochloride 10 mg (all endpoints). Physician-assessed secondary endpoints also showed that cyclobenzaprine hydrochloride 5 mg was associated with a greater reduction in palpable muscle spasm than placebo.

Analysis of the data from controlled studies shows that cyclobenzaprine produces clinical improvement whether or not sedation occurs.

Surveillance Program

A post-marketing surveillance program was carried out in 7,607 patients with acute musculoskeletal disorders, and included 297 patients treated with cyclobenzaprine hydrochloride 10 mg for 30 days or longer. The overall effectiveness of cyclobenzaprine was similar to that observed in the double-blind controlled studies; the overall incidence of adverse effects was less (see ADVERSE REACTIONS).

INDICATIONS AND USAGE

Cyclobenzaprine hydrochloride tablets, USP are indicated as an adjunct to rest and physical therapy for relief of muscle spasm associated with acute, painful musculoskeletal conditions.

Improvement is manifested by relief of muscle spasm and its associated signs and symptoms, namely, pain, tenderness, limitation of motion, and restriction in activities of daily living.

Cyclobenzaprine hydrochloride tablets should be used only for short periods (up to 2 or 3 weeks) because adequate evidence of effectiveness for more prolonged use is not available and because muscle spasm associated with acute, painful musculoskeletal conditions is generally of short duration and specific therapy for longer periods is seldom warranted.

Cyclobenzaprine hydrochloride tablets have not been found effective in the treatment of spasticity associated with cerebral or spinal cord disease, or in children with cerebral palsy.

CONTRAINDICATIONS

Hypersensitivity to any component of this product.

Concomitant use of monoamine oxidase (MAO) inhibitors or within 14 days after their discontinuation. Hyperpyretic crisis seizures and deaths have occurred in patients receiving cyclobenzaprine (or structurally similar tricyclic antidepressants) concomitantly with MAO inhibitor drugs.

Acute recovery phase of myocardial infarction, and patients with arrhythmias, heart block or conduction disturbances, or congestive heart failure.

Hyperthyroidism.

WARNINGS

Serotonin Syndrome

The development of a potentially life-threatening serotonin syndrome has been reported with cyclobenzaprine hydrochloride when used in combination with other drugs, such as selective serotonin reuptake inhibitors (SSRIs), serotonin norepinephrine reuptake inhibitors (SNRIs), tricyclic antidepressants (TCAs), tramadol, bupropion, meperidine, verapamil, or (MAO) inhibitors. The concomitant use of cyclobenzaprine hydrochloride with MAO inhibitors is contraindicated (see CONTRAINDICATIONS). Serotonin syndrome symptoms may include mental status changes (e.g., confusion, agitation, hallucinations), autonomic instability (e.g., diaphoresis, tachycardia, labile blood pressure, hyperthermia), neuromuscular abnormalities (e.g., tremor, ataxia, hyperreflexia, clonus, muscle rigidity), and/or gastrointestinal symptoms (e.g., nausea, vomiting, diarrhea). Treatment with cyclobenzaprine hydrochloride and any concomitant serotonergic agents should be discontinued immediately if the above reactions occur and supportive symptomatic treatment should be initiated. If concomitant treatment with cyclobenzaprine hydrochloride and other serotonergic drugs is clinically warranted, careful observation is advised, particularly during treatment initiation or dose increases (see PRECAUTIONS: Drug Interactions).

Cyclobenzaprine is closely related to the tricyclic antidepressants, e.g., amitriptyline and imipramine. In short term studies for indications other than muscle spasm associated with acute musculoskeletal conditions, and usually at doses somewhat greater than those recommended for skeletal muscle spasm, some of the more serious central nervous system reactions noted with the tricyclic antidepressants have occurred (see WARNINGS, below, and ADVERSE REACTIONS).

Tricyclic antidepressants have been reported to produce arrhythmias, sinus tachycardia, prolongation of the conduction time leading to myocardial infarction and stroke.

Cyclobenzaprine may enhance the effects of alcohol, barbiturates, and other CNS depressants.

PRECAUTIONS

General

Because of its atropine-like action, cyclobenzaprine should be used with caution in patients with a history of urinary retention, angle-closure glaucoma, increased intraocular pressure, and in patients taking anticholinergic medication.

Impaired Hepatic Function

The plasma concentration of cyclobenzaprine is increased in patients with hepatic impairment (see CLINICAL PHARMACOLOGY: Pharmacokinetics: Hepatic Impairment). These patients are generally more susceptible to drugs with potentially sedating effects, including cyclobenzaprine. Cyclobenzaprine hydrochloride should be used with caution in subjects with mild hepatic impairment starting with a 5 mg dose and titrating slowly upward. Due to the lack of data in subjects with more severe hepatic insufficiency, the use of cyclobenzaprine in subjects with moderate to severe impairment is not recommended.

Information for Patients

Cyclobenzaprine, especially when used with alcohol or other CNS depressants, may impair mental and/or physical abilities required for performance of hazardous tasks, such as operating machinery or driving a motor vehicle. In the elderly, the frequency and severity of adverse events associated with the use of cyclobenzaprine, with or without concomitant medications, is increased. In elderly patients, cyclobenzaprine hydrochloride should be initiated with a 5 mg dose and titrated slowly upward.

Patients should be cautioned about the risk of serotonin syndrome with the concomitant use of cyclobenzaprine hydrochloride and other drugs, such as SSRIs, SNRIs, TCAs, tramadol, bupropion, meperidine, verapamil or MAO inhibitors. Patients should be advised of the signs and symptoms of serotonin syndrome, and be instructed to seek medical care immediately if they experience these symptoms (see WARNINGSand PRECAUTIONS: Drug Interactions).

Drug Interactions

Cyclobenzaprine may have life-threatening interactions with MAO inhibitors (see CONTRAINDICATIONS). Postmarketing cases of serotonin syndrome have been reported during combined use of cyclobenzaprine hydrochloride and other drugs, such as SSRIs, SNRIs, TCAs, tramadol, bupropion, meperidine, verapamil or MAO inhibitors. If concomitant treatment with cyclobenzaprine hydrochloride and other serotonergic drugs is clinically warranted, careful observation is advised, particularly during treatment initiation or dose increases (see WARNINGS).

Cyclobenzaprine may enhance the effects of alcohol, barbiturates, and other CNS depressants.

Tricyclic antidepressants may block the antihypertensive action of guanethidine and similarly acting compounds.

Tricyclic antidepressants may enhance the seizure risk in patients taking tramadol.

Carcinogenesis, Mutagenesis, Impairment of Fertility

In rats treated with cyclobenzaprine for up to 67 weeks at doses of approximately 5 to 40 times the maximum recommended human dose, pale, sometimes enlarged, livers were noted and there was a dose-related hepatocyte vacuolation with lipidosis. In the higher dose groups this microscopic change was seen after 26 weeks and even earlier in rats which died prior to 26 weeks; at lower doses, the change was not seen until after 26 weeks.

Cyclobenzaprine did not affect the onset, incidence or distribution of neoplasia in an 81-week study in the mouse or in a 105-week study in the rat.

At oral doses of up to 10 times the human dose, cyclobenzaprine did not adversely affect the reproductive performance or fertility of male or female rats. Cyclobenzaprine did not demonstrate mutagenic activity in the male mouse at dose levels of up to 20 times the human dose.

Pregnancy

Teratogenic Effects. Pregnancy Category B

Reproduction studies have been performed in rats, mice and rabbits at doses up to 20 times the human dose, and have revealed no evidence of impaired fertility or harm to the fetus due to cyclobenzaprine. There are, however, no adequate and well-controlled studies in pregnant women. Because animal reproduction studies are not always predictive of human response, this drug should be used during pregnancy only if clearly needed.

Nursing Mothers

It is not known whether this drug is excreted in human milk. Because cyclobenzaprine is closely related to the tricyclic antidepressants, some of which are known to be excreted in human milk, caution should be exercised when cyclobenzaprine hydrochloride is administered to a nursing woman.

Pediatric Use

Safety and effectiveness of cyclobenzaprine in pediatric patients below 15 years of age have not been established.

Use in the Elderly

The plasma concentration of cyclobenzaprine is increased in the elderly (see CLINICAL PHARMACOLOGY: Pharmacokinetics: Elderly). The elderly may also be more at risk for CNS adverse events such as hallucinations and confusion, cardiac events resulting in falls or other sequelae, drug-drug and drug-disease interactions. For these reasons, in the elderly, cyclobenzaprine should be used only if clearly needed. In such patients cyclobenzaprine hydrochloride should be initiated with a 5 mg dose and titrated slowly upward.

ADVERSE REACTIONS

Incidence of most common adverse reactions in the two double-blind*, placebo-controlled 5 mg studies (incidence of > 3% on cyclobenzaprine hydrochloride 5 mg):

 | Cyclobenzaprine Hydrochloride 5 mg | Cyclobenzaprine Hydrochloride 10 mg | Placebo
 | N = 464 | N = 249 | N = 469
Drowsiness | 29% | 38% | 10%
Dry Mouth | 21% | 32% | 7%
Fatigue | 6% | 6% | 3%
Headache | 5% | 5% | 8%

*Note: Cyclobenzaprine hydrochloride 10 mg data are from one clinical trial. Cyclobenzaprine hydrochloride 5 mg and placebo data are from two studies.

Adverse reactions which were reported in 1% to 3% of the patients were: abdominal pain, acid regurgitation, constipation, diarrhea, dizziness, nausea, irritability, mental acuity decreased, nervousness, upper respiratory infection, and pharyngitis.

The following list of adverse reactions is based on the experience in 473 patients treated with cyclobenzaprine hydrochloride 10 mg in additional controlled clinical studies, 7,607 patients in the postmarketing surveillance program, and reports received since the drug was marketed. The overall incidence of adverse reactions among patients in the surveillance program was less than the incidence in the controlled clinical studies.

The adverse reactions reported most frequently with cyclobenzaprine were drowsiness, dry mouth and dizziness. The incidence of these common adverse reactions was lower in the surveillance program than in the controlled clinical studies:

 | Clinical Studies with Cyclobenzaprine hydrochloride 10 mg | Surveillance Program with Cyclobenzaprine hydrochloride 10 mg
Drowsiness | 39% | 16%
Dry Mouth | 27% | 7%
Dizziness | 11% | 3%

Among the less frequent adverse reactions, there was no appreciable difference in incidence in controlled clinical studies or in the surveillance program. Adverse reactions which were reported in 1% to 3% of the patients were: fatigue/tiredness, asthenia, nausea, constipation, dyspepsia, unpleasant taste, blurred vision, headache, nervousness, and confusion.

The following adverse reactions have been reported in postmarketing experience or with an incidence of less than 1% of patients in clinical trials with the 10 mg tablet:

Body as a Whole:Syncope; malaise.

Cardiovascular:Tachycardia; arrhythmia; vasodilatation; palpitation; hypotension.

Digestive:Vomiting; anorexia; diarrhea; gastrointestinal pain; gastritis; thirst; flatulence; edema of the tongue; abnormal liver function and rare reports of hepatitis, jaundice and cholestasis.

Hypersensitivity:Anaphylaxis; angioedema; pruritus; facial edema; urticaria; rash.

Musculoskeletal:Local weakness.

Nervous System and Psychiatric:Seizures; ataxia; vertigo; dysarthria; tremors; hypertonia; convulsions; muscle twitching; disorientation; insomnia; depressed mood; abnormal sensations; anxiety; agitation; psychosis; abnormal thinking and dreaming; hallucinations; excitement; paresthesia; diplopia, serotonin syndrome.

Skin:Sweating.

Special Senses:Ageusia; tinnitus.

Urogenital:Urinary frequency and/or retention.

Causal Relationship Unknown

Other reactions, reported rarely for cyclobenzaprine under circumstances where a causal relationship could not be established or reported for other tricyclic drugs, are listed to serve as alerting information to physicians:

Body as a Whole:Chest pain; edema.

Cardiovascular:Hypertension; myocardial infarction; heart block; stroke.

Digestive:Paralytic ileus; tongue discoloration; stomatitis; parotid swelling.

Endocrine:Inappropriate ADH syndrome.

Hematic and Lymphatic:Purpura; bone marrow depression; leukopenia; eosinophilia; thrombocytopenia.

Metabolic, Nutritional and Immune:Elevation and lowering of blood sugar levels; weight gain or loss.

Musculoskeletal:Myalgia.

Nervous System and Psychiatric:Decreased or increased libido; abnormal gait; delusions; aggressive behavior; paranoia; peripheral neuropathy; Bell's palsy; alteration in EEG patterns; extrapyramidal symptoms.

Respiratory:Dyspnea.

Skin:Photosensitization; alopecia.

Urogenital:Impaired urination; dilatation of urinary tract; impotence; testicular swelling; gynecomastia; breast enlargement; galactorrhea.

DRUG ABUSE AND DEPENDENCE

Pharmacologic similarities among the tricyclic drugs require that certain withdrawal symptoms be considered when cyclobenzaprine is administered, even though they have not been reported to occur with this drug. Abrupt cessation of treatment after prolonged administration rarely may produce nausea, headache, and malaise. These are not indicative of addiction.

OVERDOSAGE

Although rare, deaths may occur from overdosage with cyclobenzaprine. Multiple drug ingestion (including alcohol) is common in deliberate cyclobenzaprine overdose. As management of overdose is complex and changing, it is recommended that the physician contact a poison control center for current information on treatment. Signs and symptoms of toxicity may develop rapidly after cyclobenzaprine overdose; therefore, hospital monitoring is required as soon as possible. The acute oral LD50of cyclobenzaprine is approximately 338 and 425 mg/kg in mice and rats, respectively.

Manifestations

The most common effects associated with cyclobenzaprine overdose are drowsiness and tachycardia. Less frequent manifestations include tremor, agitation, coma, ataxia, hypertension, slurred speech, confusion, dizziness, nausea, vomiting, and hallucinations. Rare but potentially critical manifestations of overdose are cardiac arrest, chest pain, cardiac dysrhythmias, severe hypotension, seizures, and neuroleptic malignant syndrome.

Changes in the electrocardiogram, particularly in QRS axis or width, are clinically significant indicators of cyclobenzaprine toxicity. Other potential effects of overdosage include any of the symptoms listed under ADVERSE REACTIONS.

Management

General

As management of overdose is complex and changing, it is recommended that the physician contact a poison control center for current information on treatment.

In order to protect against the rare but potentially critical manifestations described above, obtain an ECG and immediately initiate cardiac monitoring. Protect the patient's airway, establish an intravenous line and initiate gastric decontamination. Observation with cardiac monitoring and observation for signs of CNS or respiratory depression, hypotension, cardiac dysrhythmias and/or conduction blocks, and seizures is necessary. If signs of toxicity occur at any time during this period, extended monitoring is required. Monitoring of plasma drug levels should not guide management of the patient. Dialysis is probably of no value because of low plasma concentrations of the drug.

Gastrointestinal Decontamination

All patients suspected of an overdose with cyclobenzaprine should receive gastrointestinal decontamination. This should include large volume gastric lavage followed by activated charcoal. If consciousness is impaired, the airway should be secured prior to lavage and emesis is contraindicated.

Cardiovascular

A maximal limb-lead QRS duration of ≥ 0.10 seconds may be the best indication of the severity of the overdose. Serum alkalinization, to a pH of 7.45 to 7.55, using intravenous sodium bicarbonate and hyperventilation (as needed), should be instituted for patients with dysrhythmias and/or QRS widening. A pH > 7.60 or a pCO2< 20 mmHg is undesirable. Dysrhythmias unresponsive to sodium bicarbonate therapy/hyperventilation may respond to lidocaine, bretylium or phenytoin. Type 1A and 1C antiarrhythmics are generally contraindicated (e.g., quinidine, disopyramide, and procainamide).

CNS

In patients with CNS depression, early intubation is advised because of the potential for abrupt deterioration. Seizures should be controlled with benzodiazepines or, if these are ineffective, other anticonvulsants (e.g., phenobarbital, phenytoin). Physostigmine is not recommended except to treat life-threatening symptoms that have been unresponsive to other therapies, and then only in close consultation with a poison control center.

Psychiatric Follow-up

Since overdosage is often deliberate, patients may attempt suicide by other means during the recovery phase. Psychiatric referral may be appropriate.

Pediatric Management

The principles of management of child and adult overdosages are similar. It is strongly recommended that the physician contact the local poison control center for specific pediatric treatment.

DOSAGE AND ADMINISTRATION

For most patients, the recommended dose of cyclobenzaprine hydrochloride tablets is 5 mg three times a day. Based on individual patient response, the dose may be increased to 10 mg three times a day. Use of cyclobenzaprine hydrochloride tablets for periods longer than 2 or 3 weeks is not recommended (see INDICATIONS AND USAGE).

Less frequent dosing should be considered for hepatically impaired or elderly patients (see PRECAUTIONS: Impaired Hepatic Function, and Use in the Elderly).

HOW SUPPLIED

Cyclobenzaprine Hydrochloride Tablets, USP are available containing 10 mg of cyclobenzaprine hydrochloride, USP.

The 10 mg tablets are orange-yellow film-coated, round tablets debossed with 022 on one side and plain on other side. They are available as follows:

NDC: 70518-3415-00

NDC: 70518-3415-01

NDC: 70518-3415-02

NDC: 70518-3415-03

NDC: 70518-3415-04

NDC: 70518-3415-05

NDC: 70518-3415-06

PACKAGING: 30 in 1 BLISTER PACK

PACKAGING: 90 in 1 BOTTLE PLASTIC

PACKAGING: 30 in 1 BOTTLE PLASTIC

PACKAGING: 12 in 1 BOTTLE PLASTIC

PACKAGING: 90 in 1 BOTTLE PLASTIC

PACKAGING: 14 in 1 BOTTLE PLASTIC

PACKAGING: 20 in 1 BOTTLE PLASTIC

Store at 20°C to 25°C (68°F to 77°F). [See USP Controlled Room Temperature.]

Dispense in a tight, light-resistant container as defined in the USP using a child-resistant closure.

Repackaged and Distributed By:

Remedy Repack, Inc.

625 Kolter Dr. Suite #4 Indiana, PA 1-724-465-8762

PACKAGE LABEL

DRUG: CYCLOBENZAPRINE HYDROCHLORIDE

GENERIC: cyclobenzaprine hydrochloride

DOSAGE: TABLET, FILM COATED

ADMINSTRATION: ORAL

NDC: 70518-3415-0

NDC: 70518-3415-1

NDC: 70518-3415-2

NDC: 70518-3415-3

NDC: 70518-3415-4

NDC: 70518-3415-5

NDC: 70518-3415-6

COLOR: orange

SHAPE: ROUND

SCORE: No score

SIZE: 8 mm

IMPRINT: 022

PACKAGING: 330 in 1 BLISTER PACK

PACKAGING: 90 in 1 BOTTLE PLASTIC

PACKAGING: 30 in 1 BOTTLE PLASTIC

PACKAGING: 12 in 1 BOTTLE PLASTIC

PACKAGING: 90 in 1 BOTTLE PLASTIC

PACKAGING: 14 in 1 BOTTLE PLASTIC

PACKAGING: 20 in 1 BOTTLE PLASTIC

ACTIVE INGREDIENT(S):

- CYCLOBENZAPRINE HYDROCHLORIDE 10mg in 1

INACTIVE INGREDIENT(S):

- ANHYDROUS LACTOSE
- CELLULOSE, MICROCRYSTALLINE
- CROSPOVIDONE (15 MPA.S AT 5%)
- HYPROMELLOSE, UNSPECIFIED
- MAGNESIUM STEARATE
- POLYETHYLENE GLYCOL 400
- POLYSORBATE 80
- SILICON DIOXIDE
- STARCH, CORN
- TITANIUM DIOXIDE
- D&C YELLOW NO. 10
- FD&C YELLOW NO. 6